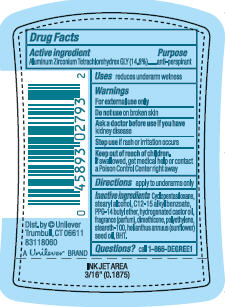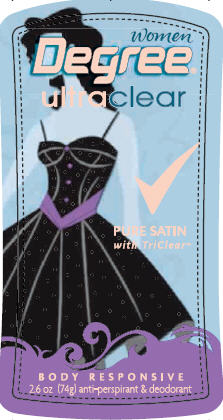 DRUG LABEL: Degree UltraClear Pure Satin
NDC: 64942-0779 | Form: STICK
Manufacturer: Conopco Inc. d/b/a Unilever
Category: otc | Type: HUMAN OTC DRUG LABEL
Date: 20100222

ACTIVE INGREDIENTS: Aluminum Zirconium  Tetrachlorohydrex GLY 14.8 g/100 g

PDP and drug facts for Degree UltraClear Pure Satin AP and Deodorant

Active Ingredient Purpose
Aluminum Zirconium Tetrachlorohydrex GLY (14.8%).....anti-perspirant

Warnings
For external use only

Do not use on broken skin

Ask a doctor before use if you have kidney disease

Stop use if rash or irritation occurs

Keep out of reach of children. If swallowed, get medical help or contact a Poison Control Center right away

INACTIVE INGREDIENT

Cyclopentasiloxane, Stearyl Alcohol, C12-15 Alkyl Benzoate, PPG-14 Butyl Ether, Hydrogenated Castor Oil, Fragrance (Parfum), Dimethicone, Polyethylene, Steareth-100, Helianthus Annuus (Sunflower) Seed Oil, BHT

Questions? call 1-866 DEGREE1

PACKAGE LABEL

PDP 2.6 oz front

PACKAGE LABEL

PDP 2.6 oz. back